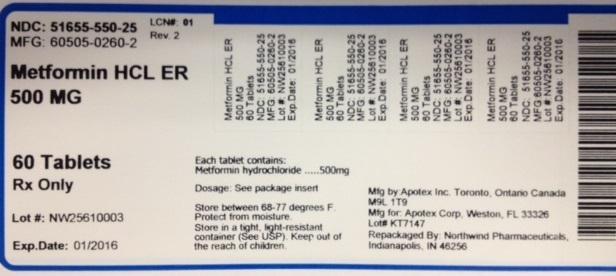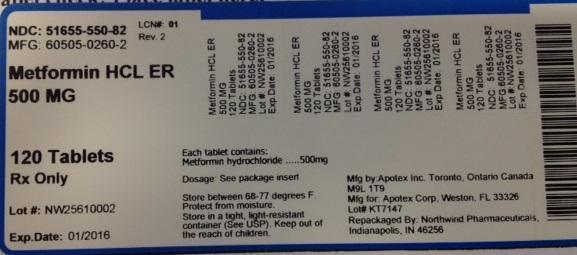 DRUG LABEL: Metformin hydrochloride
NDC: 51655-550 | Form: TABLET, EXTENDED RELEASE
Manufacturer: Northwind Pharmaceuticals
Category: prescription | Type: HUMAN PRESCRIPTION DRUG LABEL
Date: 20140930

ACTIVE INGREDIENTS: METFORMIN HYDROCHLORIDE 500 mg/1 1

Metformin Hydrochloride Extended Release 500 MG

Patient Information

Information for Patients

Patients should be informed of the potential risks and benefits of metformin and of alternative modes of therapy. They should also be informed about the importance of adherence to dietary instructions, of a regular exercise program, and of regular testing of blood glucose, glycosylated hemoglobin, renal function, and hematologic parameters.

The risks of lactic acidosis, its symptoms, and conditions that predispose to its development, as noted in the WARNINGS and PRECAUTIONS sections, should be explained to patients. Patients should be advised to discontinue metformin immediately and to promptly notify their health practitioner if unexplained hyperventilation, myalgia, malaise, unusual somnolence, or other nonspecific symptoms occur. Once a patient is stabilized on any dose level of metformin, gastrointestinal symptoms, which are common during initiation of metformin therapy, are unlikely to be drug related. Later occurrence of gastrointestinal symptoms could be due to lactic acidosis or other serious disease.

Patients should be counselled against excessive alcohol intake, either acute or chronic, while receiving metformin.

Metformin alone does not usually cause hypoglycemia, although it may occur when metformin is used in conjunction with oral sulfonylureas and insulin. When initiating combination therapy, the risks of hypoglycemia, its symptoms and treatment, and conditions that predispose to its development should be explained to patients and responsible family members.

Patients should be informed that metformin hydrochloride extended-release tablets must be swallowed whole and not crushed or chewed, and that the inactive ingredients may occasionally be eliminated in the feces as a soft mass that may resemble the original tablet.

Laboratory Tests

Response to all diabetic therapies should be monitored by periodic measurements of fasting blood glucose and glycosylated hemoglobin levels, with a goal of decreasing these levels toward the normal range. During initial dose titration, fasting glucose can be used to determine the therapeutic response. Thereafter, both glucose and glycosylated hemoglobin should be monitored. Measurements of glycosylated hemoglobin may be especially useful for evaluating long-term control.

Initial and periodic monitoring of hematologic parameters (e.g., hemoglobin/hematocrit and red blood cell indices) and renal function (serum creatinine) should be performed, at least on an annual basis. While megaloblastic anemia has rarely been seen with metformin hydrochloride tablets therapy, if this is suspected, vitamin B12 deficiency should be excluded.

Drug Interactions

Drug Interactions (clinical evaluation of drug interactions done with metformin hydrochloride tablets)

Glyburide: In a single-dose interaction study in type 2 diabetes patients, co-administration of metformin and glyburide did not result in any changes in either metformin pharmacokinetics or pharmacodynamics. Decreases in glyburide AUC and Cmax were observed, but were highly variable. The single-dose nature of this study and the lack of correlation between glyburide blood levels and pharmacodynamic effects, makes the clinical significance of this interaction uncertain (see DOSAGE AND ADMINISTRATION: Concomitant Metformin and Oral Sulfonylurea Therapy in Adult Patients).

Furosemide: A single-dose, metformin-furosemide drug interaction study in healthy subjects demonstrated that pharmacokinetic parameters of both compounds were affected by co-administration. Furosemide increased the metformin plasma and blood Cmax by 22% and blood AUC by 15%, without any significant change in metformin renal clearance. When administered with metformin, the Cmax and AUC of furosemide were 31% and 12% smaller, respectively, than when administered alone, and the terminal half-life was decreased by 32%, without any significant change in furosemide renal clearance. No information is available about the interaction of metformin and furosemide when coadministered chronically.

Nifedipine: A single-dose, metformin-nifedipine drug interaction study in normal healthy volunteers demonstrated that co-administration of nifedipine increased plasma metformin Cmax and AUC by 20% and 9%, respectively, and increased the amount excreted in the urine. Tmax and half-life were unaffected. Nifedipine appears to enhance the absorption of metformin. Metformin had minimal effects on nifedipine.

Cationic drugs: Cationic drugs (e.g., amiloride, digoxin, morphine, procainamide, quinidine, quinine, ranitidine, triamterene, trimethoprim, or vancomycin) that are eliminated by renal tubular secretion theoretically have the potential for interaction with metformin by competing for common renal tubular transport systems. Such interaction between metformin and oral cimetidine has been observed in normal healthy volunteers in both single- and multiple-dose, metformin-cimetidine drug interaction studies, with a 60% increase in peak metformin plasma and whole blood concentrations and a 40% increase in plasma and whole blood metformin AUC. There was no change in elimination half-life in the single-dose study. Metformin had no effect on cimetidine pharmacokinetics. Although such interactions remain theoretical (except for cimetidine), careful patient monitoring and dose adjustment of metformin and/or the interfering drug is recommended in patients who are taking cationic medications that are excreted via the proximal renal tubular secretory system.

Other: Certain drugs tend to produce hyperglycemia and may lead to loss of glycemic control. These drugs include the thiazides and other diuretics, corticosteroids, phenothiazines, thyroid products, estrogens, oral contraceptives, phenytoin, nicotinic acid, sympathomimetics, calcium channel blocking drugs, and isoniazid. When such drugs are administered to a patient receiving metformin, the patient should be closely observed for loss of blood glucose control. When such drugs are withdrawn from a patient receiving metformin, the patient should be observed closely for hypoglycemia.

In healthy volunteers, the pharmacokinetics of metformin and propranolol, and metformin and ibuprofen were not affected when coadministered in single-dose interaction studies.

Metformin is negligibly bound to plasma proteins and is, therefore, less likely to interact with highly protein-bound drugs such as salicylates, sulfonamides, chloramphenicol, and prombenecid, as compared to the sulfonylureas, which are extensively bound to serum proteins.

Carcinogenesis, Mutagenesis, Impairment of Fertility

Long-term carcinogenicity studies have been performed in rats (dosing duration of 104 weeks) and mice (dosing duration of 91 weeks) at doses up to and including 900 mg/kg/day and 1500 mg/kg/day, respectively. These doses are both approximately four times the maximum recommended human daily dose of 2000 mg based on body surface area comparisons. No evidence of carcinogenicity with metformin was found in either male or female mice. Similarly, there was no tumorigenic potential observed with metformin in male rats. There was, however, an increased incidence of benign stromal uterine polyps in female rats treated with 900 mg/kg/day.

There was no evidence of a mutagenic potential of metformin in the following in vitro tests: Ames test (S. typhimurium), gene mutation test (mouse lymphoma cells), or chromosomal aberrations test (human lymphocytes). Results in the in vivo mouse micronucleus test were also negative.

Fertility of male or female rats was unaffected by metformin when administered at doses as high as 600 mg/kg/day, which is approximately three times the maximum recommended human daily dose based on body surface area comparisons.

Pregnancy

Teratogenic Effects: Pregnancy Category B

Recent information strongly suggests that abnormal blood glucose levels during pregnancy are associated with a higher incidence of congenital abnormalities. Most experts recommend that insulin be used during pregnancy to maintain blood glucose levels as close to normal as possible. Because animal reproduction studies are not always predictive of human response, metformin should not be used during pregnancy unless clearly needed.

There are no adequate and well-controlled studies in pregnant women with metformin. Metformin was not teratogenic in rats and rabbits at doses up to 600 mg/kg/day. This represents an exposure of about two and six times the maximum recommended human daily dose of 2000 mg based on body surface area comparisons for rats and rabbits, respectively. Determination of fetal concentrations demonstrated a partial placental barrier to metformin.

Nursing Mothers

Studies in lactating rats show that metformin is excreted into milk and reaches levels comparable to those in plasma. Similar studies have not been conducted in nursing mothers. Because the potential for hypoglycemia in nursing infants may exist, a decision should be made whether to discontinue nursing or to discontinue the drug, taking into account the importance of the drug to the mother. If metformin is discontinued, and if diet alone is inadequate for controlling blood glucose, insulin therapy should be considered.

Pediatric Use

The safety and effectiveness of metformin hydrochloride tablets for the treatment of type 2 diabetes have been established in pediatric patients ages 10 to 16 years (studies have not been conducted in pediatric patients below the age of 10 years). Use of metformin hydrochloride tablets in this age group is supported by evidence from adequate and well-controlled studies of metformin hydrochloride tablets in adults with additional data from a controlled clinical study in pediatric patients ages 10-16 years with type 2 diabetes, which demonstrated a similar response in glycemic control to that seen in adults. In this study, adverse effects were similar to those described in adults. A maximum daily dose of 2000 mg is recommended.

Safety and effectiveness of metformin hydrochloride extended-release tablets in pediatric patients have not been established.

Geriatric Use

Controlled clinical studies of metformin did not include sufficient numbers of elderly patients to determine whether they respond differently from younger patients, although other reported clinical experience has not identified differences in responses between the elderly and younger patients. Metformin is known to be substantially excreted by the kidney and because the risk of serious adverse reactions to the drug is greater in patients with impaired renal function, metformin should only be used in patients with normal renal function. Because aging is associated with reduced renal function, metformin should be used with caution as age increases. Care should be taken in dose selection and should be based on careful and regular monitoring of renal function. Generally, elderly patients should not be titrated to the maximum dose of metformin.

Information for Patients

For all information regarding this drug, please go to:

http://dailymed.nlm.nih.gov/dailymed/lookup.cfm?setid=e21989bb-d7ba-2dd0-d2d3-a99fc799f2a6

Package Label Principal Display

NDC: 51655-550-82

MFG: 60505-0260-2

Metformin HCL ER 500MG

120 Tablets

Rx Only

Lot#:

Exp Date:

Each tablet contains Metformin hydrochloride...500mg

Dosage: See package insert

Store between 68-77 degrees F.

Protect from moisture. Sotre in a tight, light-resistant container (See USP). Keep out of the reach of children.

Mfg by: Apotex Inc. Toronto Canada M9L 1T9

Mfg for: Apotex Corp, Weston, FL 33326

Repackaged by: Northwind Pharmaceuticals, Indianapolis, IN 46256

NDC: 51655-550-25

MFG: 60505-0260-2

Metformin HCL ER 500MG

60 Tablets

Rx Only

Lot#:

Exp Date:

Each tablet contains Metformin hydrochloride...500mg

Dosage: See package insert

Store between 68-77 degrees F.

Protect from moisture. Sotre in a tight, light-resistant container (See USP). Keep out of the reach of children.

Mfg by: Apotex Inc. Toronto Canada M9L 1T9

Mfg for: Apotex Corp, Weston, FL 33326

Repackaged by: Northwind Pharmaceuticals, Indianapolis, IN 46256